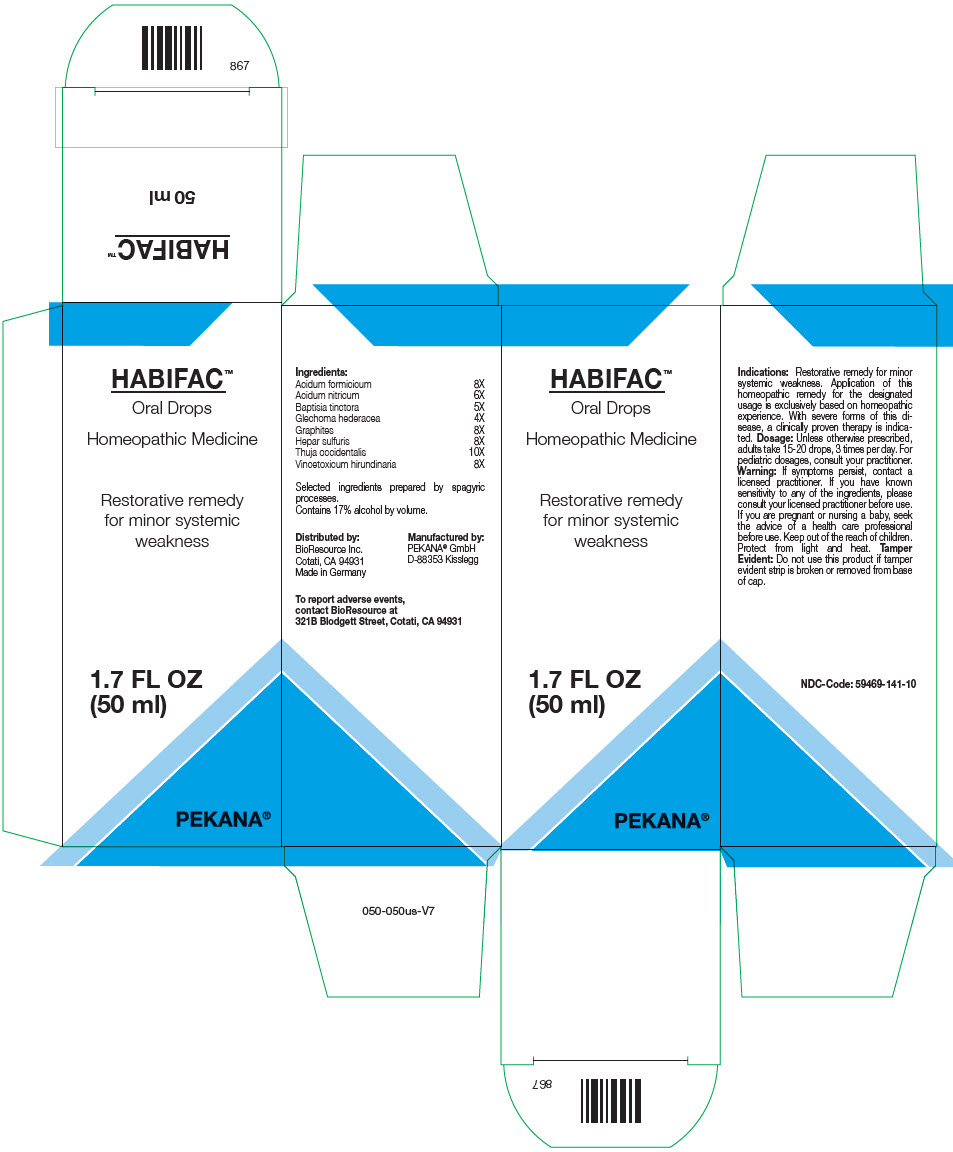 DRUG LABEL: HABIFAC
NDC: 59469-141 | Form: SOLUTION/ DROPS
Manufacturer: PEKANA Naturheilmittel GmbH
Category: homeopathic | Type: HUMAN OTC DRUG LABEL
Date: 20221215

ACTIVE INGREDIENTS: Formic Acid 8 [hp_X]/50 mL; Nitric Acid 6 [hp_X]/50 mL; Baptisia tinctoria Root 5 [hp_X]/50 mL; Graphite 8 [hp_X]/50 mL; Calcium sulfide 8 [hp_X]/50 mL; Thuja occidentalis Leafy Twig 10 [hp_X]/50 mL; Vincetoxicum Hirundinaria Leaf 8 [hp_X]/50 mL; Glechoma hederacea Flowering Top 4 [hp_X]/50 mL
INACTIVE INGREDIENTS: Water; Alcohol

HABIFAC™

ACTIVE INGREDIENT

Ingredients:
Acidum formicicum | 8X
Acidum nitricum | 6X
Baptisia tinctora | 5X
Glechoma hederacea | 4X
Graphites | 8X
Hepar sulfuris | 8X
Thuja occidentalis | 10X
Vincetoxicum hirundinaria | 8X

Selected ingredients prepared by spagyric processes.

INACTIVE INGREDIENT

Contains 17% alcohol by volume.

Indications

PURPOSE

Restorative remedy for minor systemic weakness. Application of this homeopathic remedy for the designated usage is exclusively based on homeopathic experience. With severe forms of this disease, a clinically proven therapy is indicated.

Dosage

Unless otherwise prescribed, adults take 15-20 drops, 3 times per day. For pediatric dosages, consult your practitioner.

Warning

If symptoms persist, contact a licensed practitioner. If you have known sensitivity to any of the ingredients, please consult your licensed practitioner before use. If you are pregnant or nursing a baby, seek the advice of a health care professional before use.

Keep out of the reach of children.

STORAGE AND HANDLING

Protect from light and heat.

Tamper Evident

Do not use this product if tamper evident strip is broken or removed from base of cap.

QUESTIONS

To report adverse events, contact BioResource at 321B Blodgett Street, Cotati, CA 94931

Distributed by:
BioResource Inc.
Cotati, CA 94931

Manufactured by:
PEKANA® GmbH
D-88353 Kisslegg

PRINCIPAL DISPLAY PANEL - 50 ml Bottle Box

HABIFAC™
Oral Drops

Homeopathic Medicine

Restorative remedy
for minor systemic
weakness

1.7 FL OZ
(50 ml)

PEKANA®